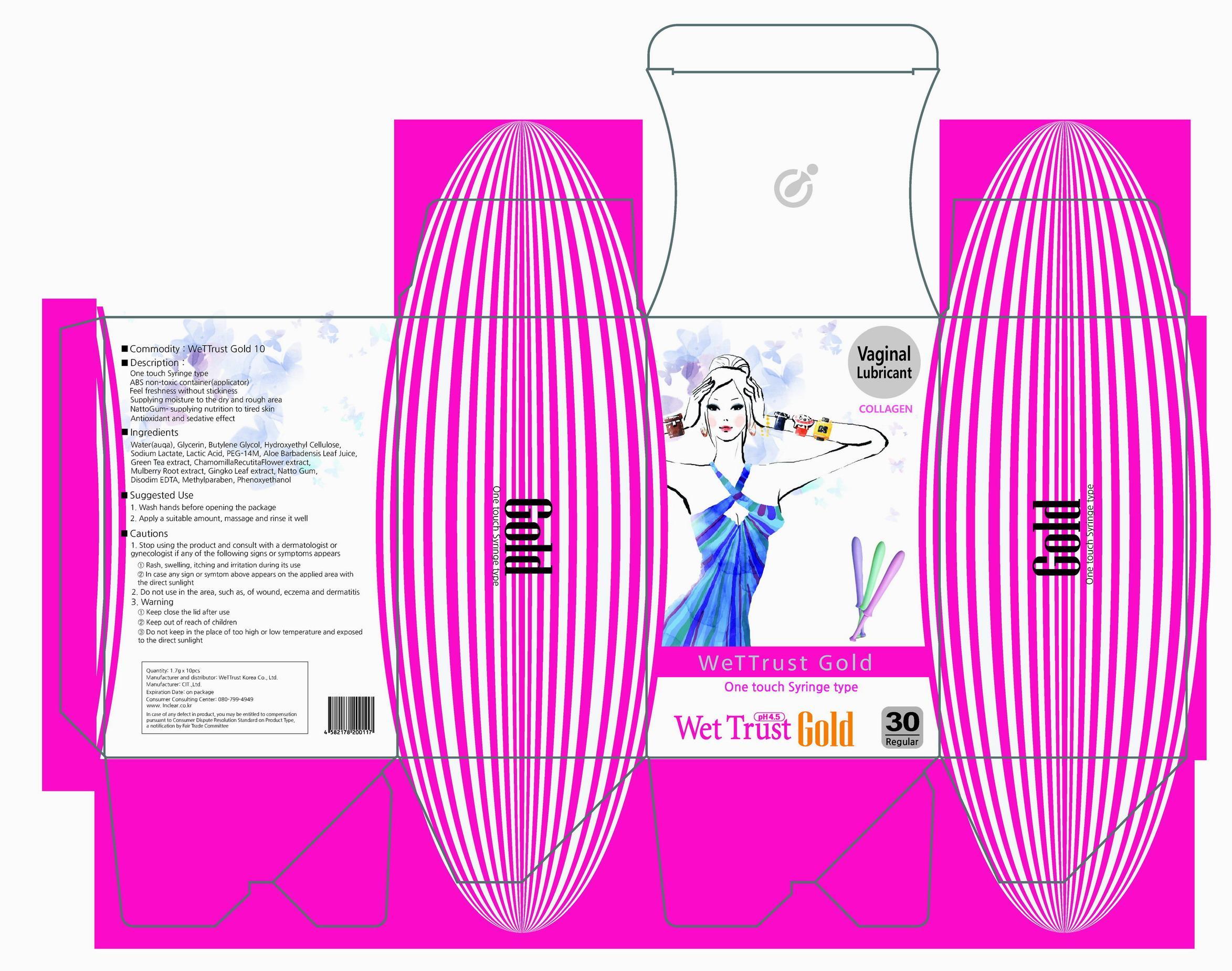 DRUG LABEL: WeTTrust Gold
NDC: 59543-1001 | Form: GEL
Manufacturer: WeTTrust Korea Co., Ltd
Category: otc | Type: HUMAN OTC DRUG LABEL
Date: 20130729

ACTIVE INGREDIENTS: Glycerin 0.17 g/1 g
INACTIVE INGREDIENTS: WATER; BUTYLENE GLYCOL; SODIUM LACTATE; LACTIC ACID; EDETATE DISODIUM; METHYLPARABEN; PHENOXYETHANOL

Drug Facts

ACTIVE INGREDIENT

glycerin

INACTIVE INGREDIENT

water, butylene glycol, hydroxyethyl cellulose, sodium lactate, lactic acid, peg-14m, aloe barbadensis leaf juice, green tea extract, chamolillaRecutitalFlower extract, mulberry root extract, gingko leaf extract, natto gum, disodium edta, methylparaben, phenoxyethanol

PURPOSE

supplying moisture to the dry and rough vagina

keep out of reach of the children

INDICATIONS AND USAGE

wash hands before opening the package
apply a suitable amount, massage and rinse it well

WARNINGS

- stop using the product and consult with a dermatologist or gynecologist if any of the following signs or symptoms appears
rash, swelling, itching and irritation during its use
in case any sign or symptom above appears on the applied area with the direct sunlight
- do not use in the area, such as, of wound, eczema and dermatitis

DOSAGE AND ADMINISTRATION

for external use only